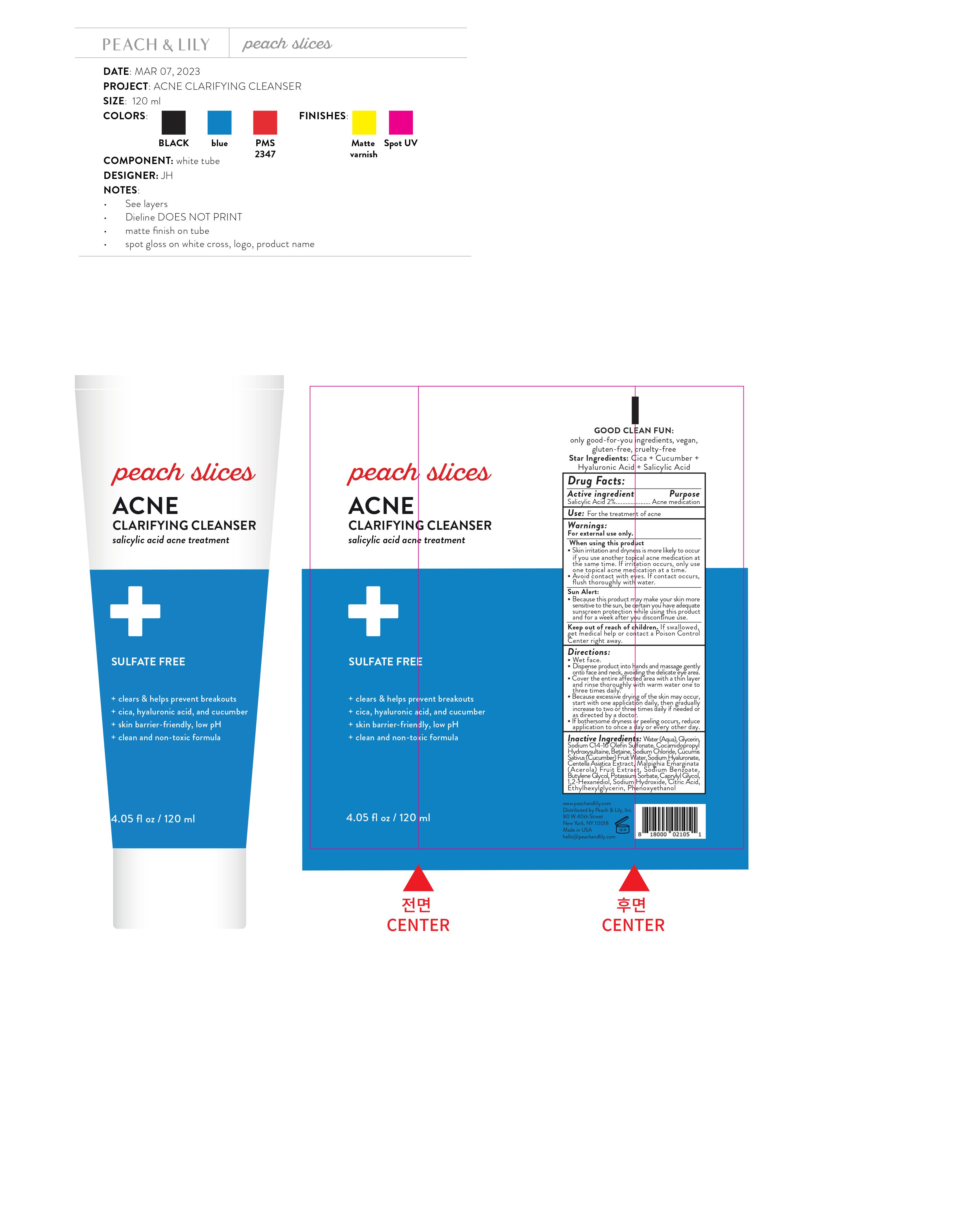 DRUG LABEL: Peach and Lily Peaches Slices Acne Clarifying Cleanser
NDC: 81515-500 | Form: GEL
Manufacturer: Peach & Lily, Inc.
Category: otc | Type: HUMAN OTC DRUG LABEL
Date: 20231028

ACTIVE INGREDIENTS: SALICYLIC ACID 20 mg/1 mL
INACTIVE INGREDIENTS: WATER; GLYCERIN; SODIUM C14-16 OLEFIN SULFONATE; COCAMIDOPROPYL HYDROXYSULTAINE; BETAINE; SODIUM CHLORIDE; CUCUMBER FRUIT OIL; HYALURONATE SODIUM; CENTELLA ASIATICA WHOLE; ACEROLA; SODIUM BENZOATE; BUTYLENE GLYCOL; POTASSIUM SORBATE; CAPRYLYL GLYCOL; 1,2-HEXANEDIOL; SODIUM HYDROXIDE; CITRIC ACID MONOHYDRATE; ETHYLHEXYLGLYCERIN; PHENOXYETHANOL

Peach & Lily Peaches Slices Acne Clarifying Cleanser

Active ingredient

Salicylic Acid 2%

Purpose

Acne medication

Use:

For the treatment of acne

Warnings:

For external use only.

When using this product

- Skin irritation and dryness is more likely to occur if you use another topical acne medication at the same time. If irritation occurs, only use one topical acne medication at a time.
- Avoid contact with eyes. If contact occurs, flush thoroughly with water.

- Because this product may make your skin more sensitive to the sun, be certain you have adequate sunscreen protection while using this product and for a week after you discontinue use.

Sun Alert:

Keep out of reach of children.

If swallowed, get medical help or contact a Poison Control Center right away.

Directions:

- Wet face.
- Dispense product into hands and massage gently onto face and neck, avoiding the delicate eye area.
- Cover the entire affected area with a thin layer and rinse thoroughly with warm water one to three times daily.
- Because excessive drying of the skin may occur, start with one application daily, then gradually increase to two or three times daily if needed or as directed by a doctor.
- If bothersome dryness or peeling occurs, reduce application to once a day or every other day.

Inactive Ingredients:

Water (Aqua), Glycerin, Sodium C14-16 Olefin Sulfonate, Cocamidopropyl Hydroxysultaine, Betaine, Sodium Chloride, Cucumis Sativus (Cucumber) Fruit Water, Sodium Hyaluronate, Centella Asiatica Extract, Malpighia Emarginata (Acerola) Fruit Extract, Sodium Benzoate, Butylene Glycol, Potassium Sorbate, Caprylyl Glycol, 1,2-Hexanediol, Sodium Hydroxide, Citric Acid, Ethylhexylglycerin, Phenoxyethanol